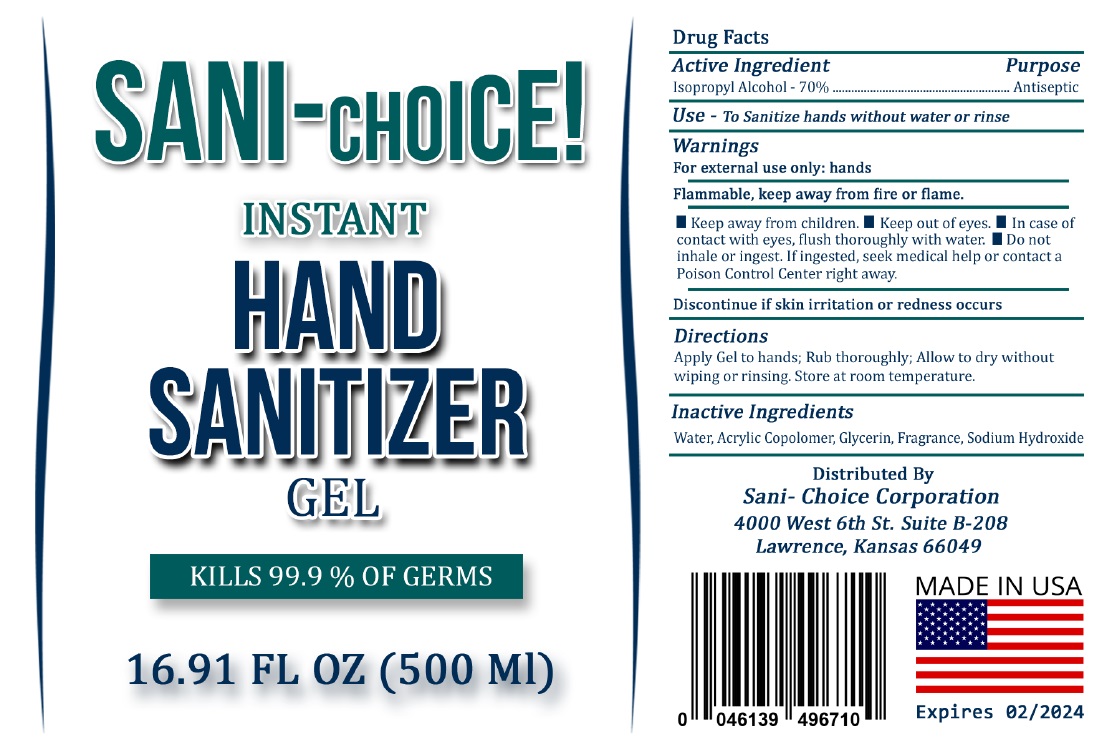 DRUG LABEL: SANI CHOICE INSTANT HAND SANITIZER
NDC: 80412-270 | Form: GEL
Manufacturer: SANI-CHOICE CORPORATION
Category: otc | Type: HUMAN OTC DRUG LABEL
Date: 20201223

ACTIVE INGREDIENTS: ISOPROPYL ALCOHOL 70 mL/100 mL
INACTIVE INGREDIENTS: WATER; ACRYLIC ACID/2-ETHYLHEXYL ACRYLATE/STYRENE COPOLYMER (500000 MW); GLYCERIN; SODIUM HYDROXIDE

SANI-CHOICE! INSTANT HAND SANITIZER GEL

Active Ingredient

Isopropyl Alcohol - 70%

Purpose

Antiseptic

Use

- To Sanitize hands without water or rinse

Warnings

For external use only: hands

Flammable, keep away from fire or flame.

• Keep out of eyes. • In case of contact with eyes, flush thoroughly with water. • Do not inhale or ingest. If ingested, seek medical help or contact a Poison Control Center right away.

Discontinue if skin irritation or redness occurs

• Keep away from children.

Directions

Apply Gel to hands; Rub thoroughly; Allow to dry without wiping or rinsing. Store at room temperature.

Inactive Ingredients

Water, Acrylic Copolomer, Glycerin, Fragrance, Sodium Hydroxide

KILLS 99.9 % OF GERMS

Distributed By

Sani- Choice Corporation

4000 West 6th st. Suite B-208

Lawrence, Kansas 66049

MADE IN USA